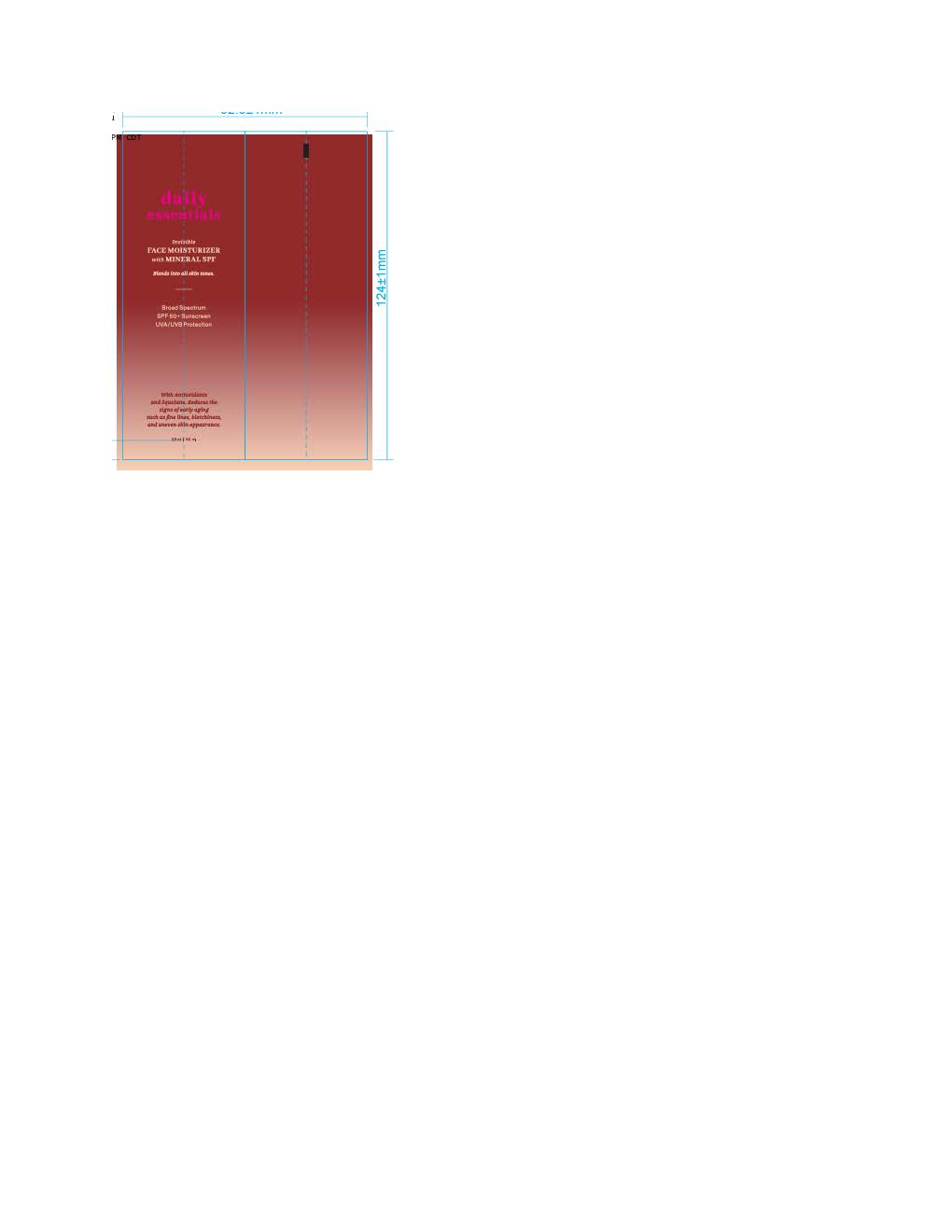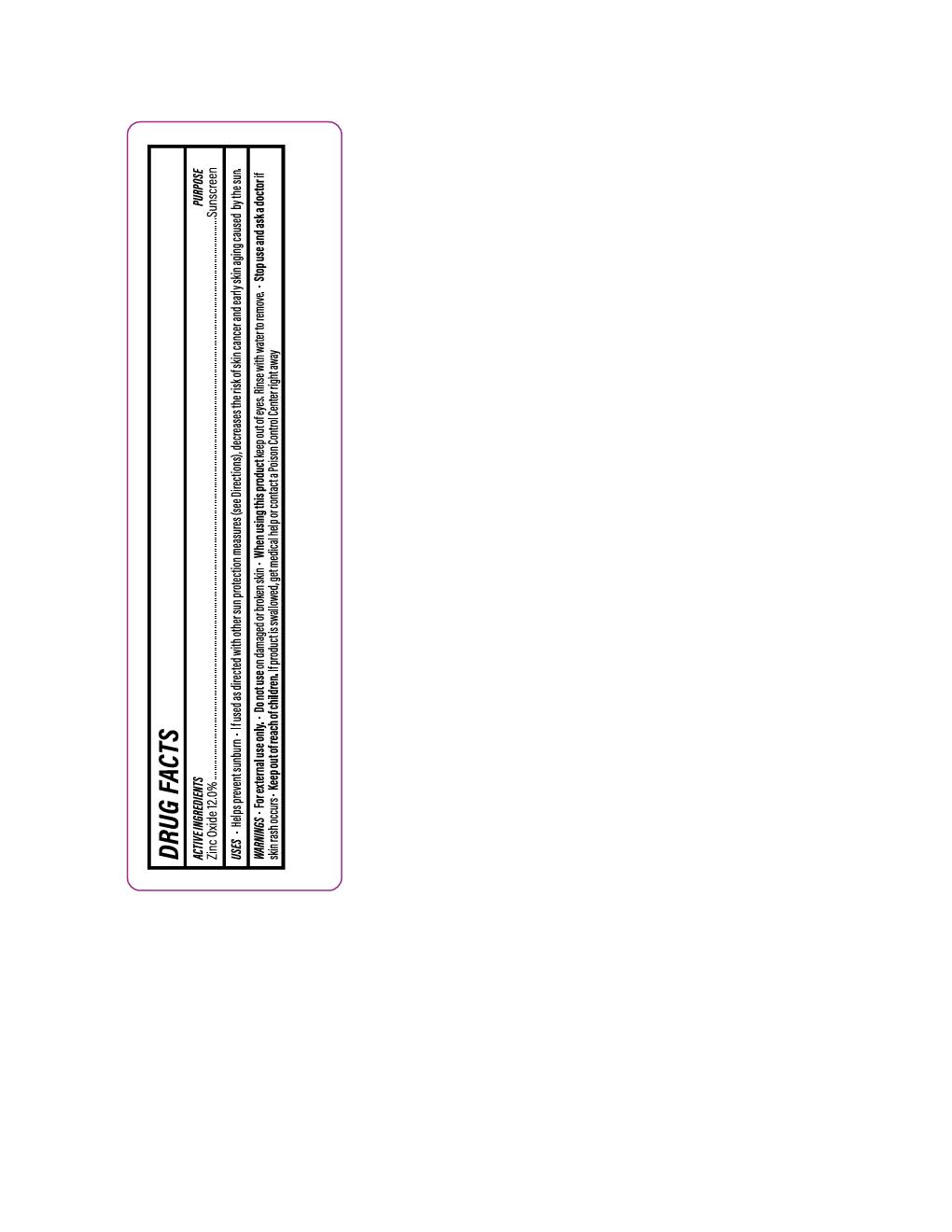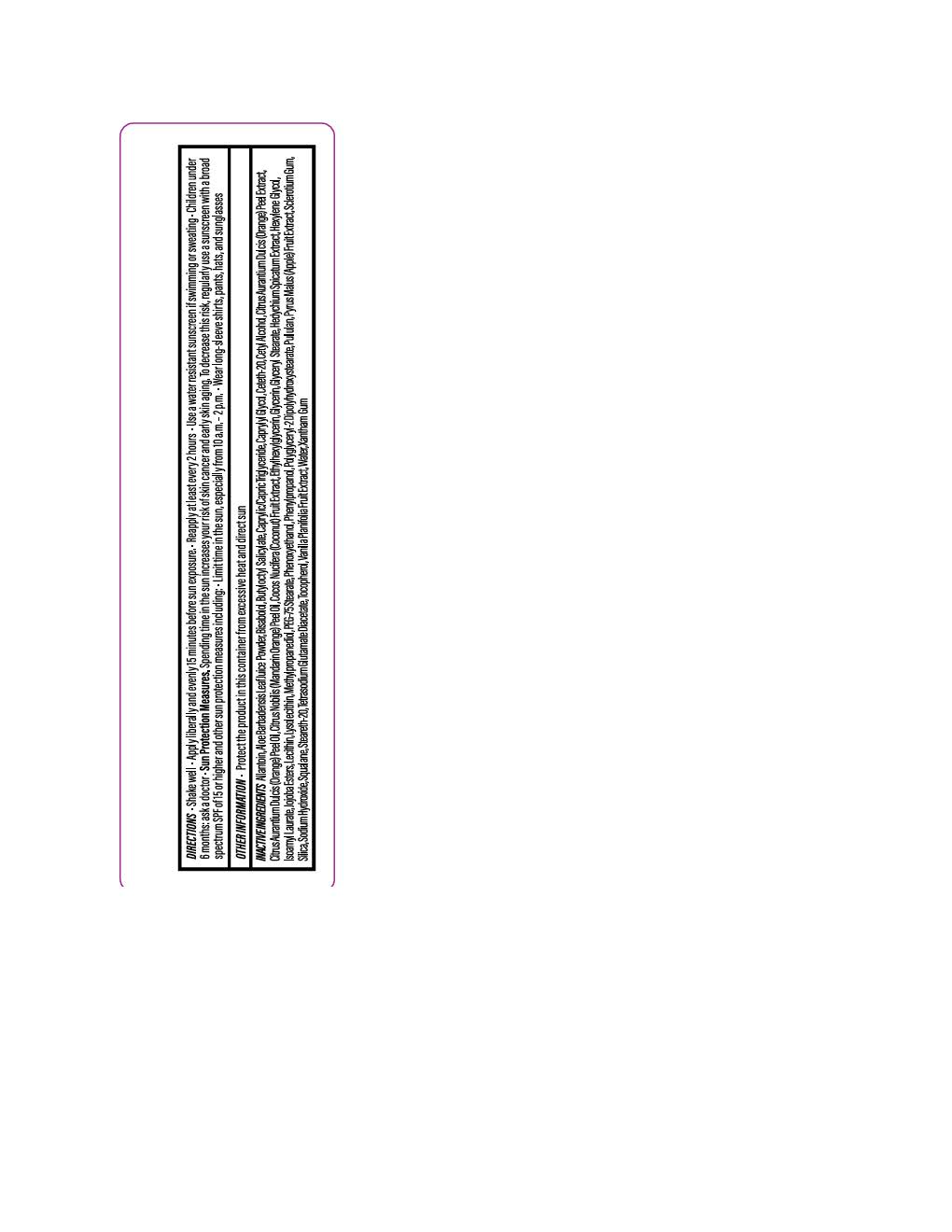 DRUG LABEL: Daily Essential Face Moisturizer
NDC: 84891-2185 | Form: LOTION
Manufacturer: Solarium Brands LLC
Category: otc | Type: HUMAN OTC DRUG LABEL
Date: 20251117

ACTIVE INGREDIENTS: ZINC OXIDE 132 mg/1 mL
INACTIVE INGREDIENTS: LECITHIN, SOYBEAN; POLYGLYCERYL-2 DIPOLYHYDROXYSTEARATE; HYDROLYZED JOJOBA ESTERS (ACID FORM); METHYLPROPANEDIOL; CAPRYLYL GLYCOL; PHENYLPROPANOL; XANTHAN GUM; ISOAMYL LAURATE; HEXYLENE GLYCOL; TOCOPHEROL; CETYL ALCOHOL; ETHYLHEXYLGLYCERIN; GLYCERIN; SILICON DIOXIDE; WATER; .ALPHA.-BISABOLOL, (+)-; BUTYLOCTYL SALICYLATE; CETETH-20; PULLULAN; SQUALANE; STEARETH-20; TETRASODIUM GLUTAMATE DIACETATE; PHENOXYETHANOL; PEG-75 STEARATE; ROSA DAMASCENA FLOWER OIL; GLYCERYL STEARATE; PYRUS MALUS (APPLE) FRUIT; LAVANDULA ANGUSTIFOLIA (LAVENDER) OIL; HELIANTHUS ANNUUS (SUNFLOWER) SEED OIL; ALLANTOIN; CAPRYLIC/CAPRIC TRIGLYCERIDE

Daily Essential Face Moisturizer